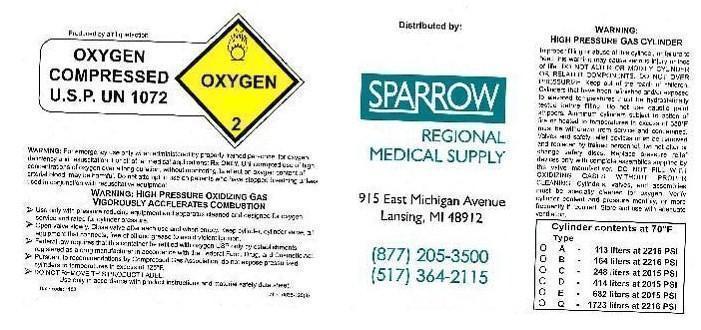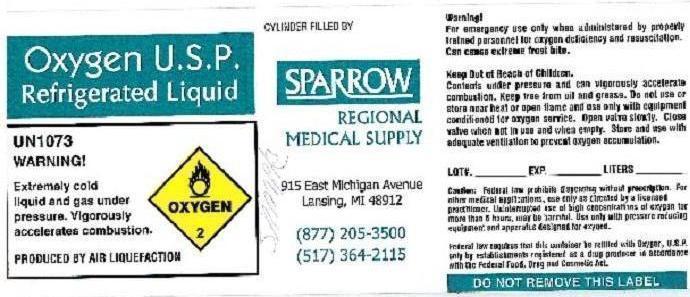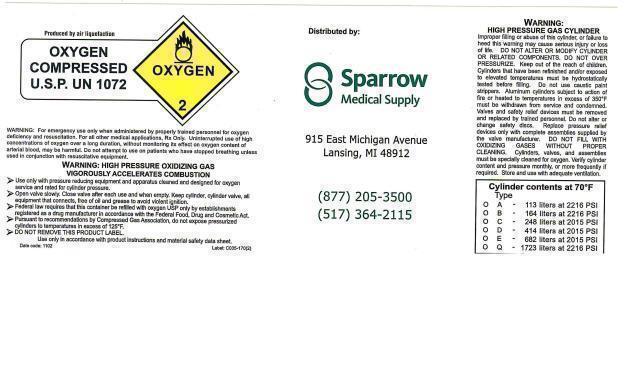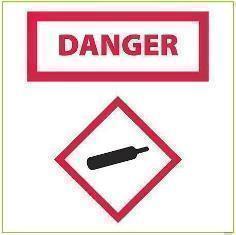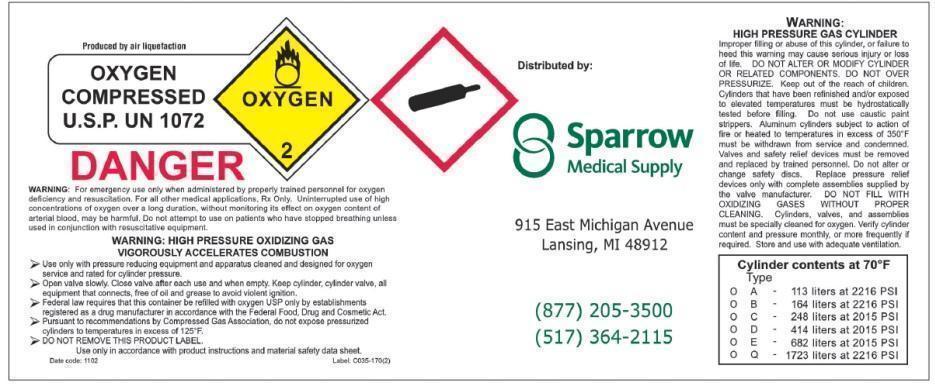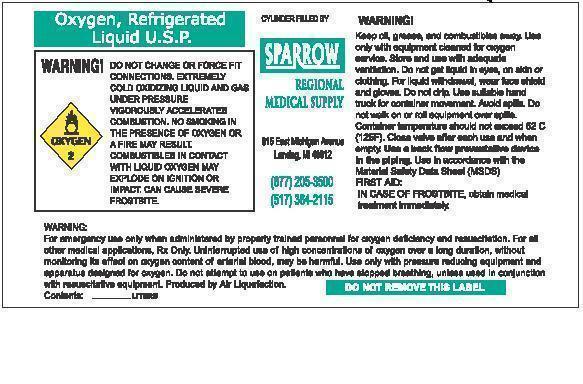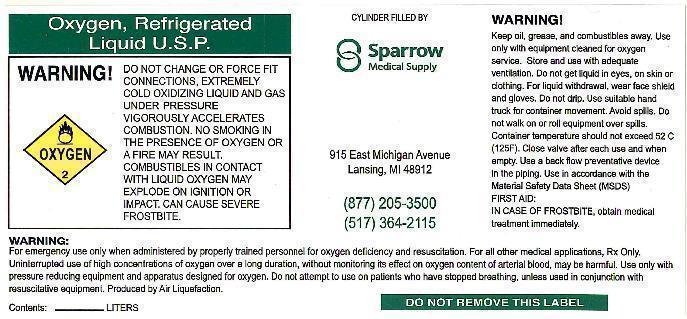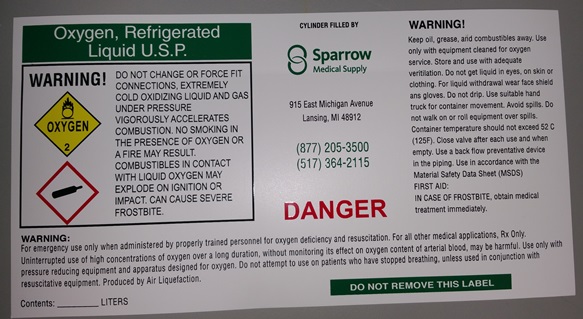 DRUG LABEL: Oxygen
NDC: 54595-001 | Form: GAS
Manufacturer: Sparrow Medical Supply L.L.C.
Category: prescription | Type: HUMAN PRESCRIPTION DRUG LABEL
Date: 20201021

ACTIVE INGREDIENTS: OXYGEN 99 mL/1 L

Labels